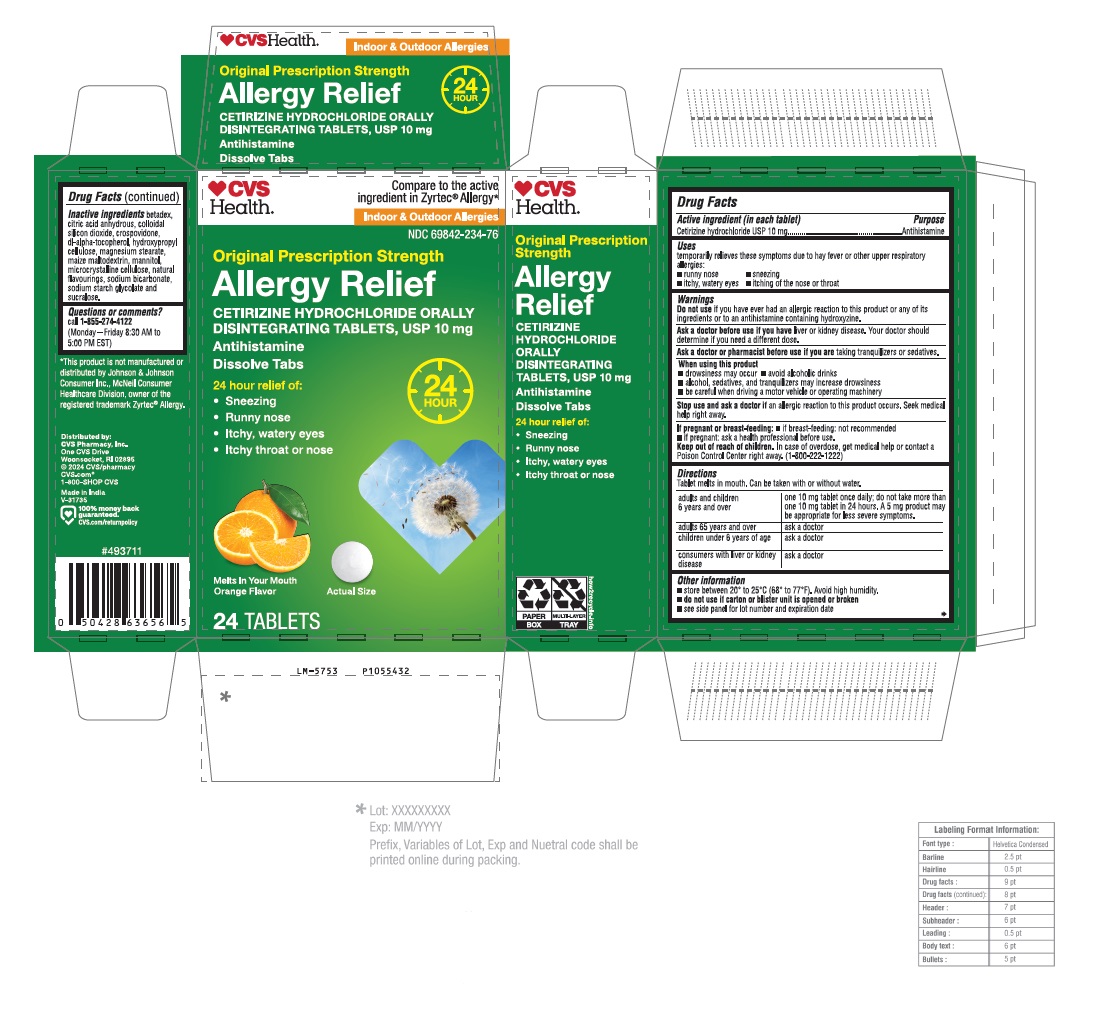 DRUG LABEL: Cetirizine Hydrochloride
NDC: 69842-234 | Form: TABLET, ORALLY DISINTEGRATING
Manufacturer: CVS Pharmacy, Inc.
Category: otc | Type: Human OTC Drug Label
Date: 20240801

ACTIVE INGREDIENTS: CETIRIZINE HYDROCHLORIDE 10 mg/1 1
INACTIVE INGREDIENTS: BETADEX; ANHYDROUS CITRIC ACID; SILICON DIOXIDE; CROSPOVIDONE (35 .MU.M); .ALPHA.-TOCOPHEROL, DL-; HYDROXYPROPYL CELLULOSE (110000 WAMW); MAGNESIUM STEARATE; MALTODEXTRIN; MANNITOL; MICROCRYSTALLINE CELLULOSE 101; MICROCRYSTALLINE CELLULOSE 102; SODIUM BICARBONATE; SODIUM STARCH GLYCOLATE TYPE A POTATO; SUCRALOSE

Drug Facts

Active ingredient (in each tablet)

Cetirizine hydrochloride USP 10 mg

Purpose

Antihistamine

Uses

temporarily relieves these symptoms due to hay fever or other upper respiratory allergies:

- runny nose
- sneezing
- itchy, watery eyes
- itching of the nose or throat

Do not use

if you have ever had an allergic reaction to this product or any of its ingredients or to an antihistamine containing hydroxyzine.

Ask a doctor before use if you have

liver or kidney disease. Your doctor should determine if you need a different dose.

Ask a doctor or pharmacist before use if you are

taking tranquilizers or sedatives.

When using this product

- drowsiness may occur
- avoid alcoholic drinks
- alcohol, sedatives, and tranquilizers may increase drowsiness
- be careful when driving a motor vehicle or operating machinery

Stop use and ask a doctor if

an allergic reaction to this product occurs. Seek medical help right away.

If pregnant or breast-feeding:

- if breast-feeding: not recommended
- if pregnant: ask a health professional before use.

Keep out of reach of children.

In case of overdose, get medical help or contact a Poison Control Center right away. (1-800-222-1222)

Directions

Tablet melts in mouth. Can be taken with or without water.

adults and children 6 years and over | one 10 mg tablet once daily; do not take more than one 10 mg tablet in 24 hours. A 5 mg product may be appropriate for less severe symptoms.
adults 65 years and over | ask a doctor
children under 6 years of age | ask a doctor
consumers with liver or kidney disease | ask a doctor

Other information

- store between 20° to 25°C (68° to 77°F). Avoid high humidity.
- do not use if carton or blister unit is opened or broken
- see side panel for lot number and expiration date

Inactive ingredients

betadex, citric acid anhydrous, colloidal silicon dioxide, crospovidone, dl-alpha-tocopherol, hydroxypropyl cellulose, magnesium stearate, maize maltodextrin, mannitol, microcrystalline cellulose, natural flavourings, sodium bicarbonate, sodium starch glycolate and sucralose.
Questions or comments?
call 1-855-274-4122 (Monday - Friday 8:30 AM to 5:00 PM EST)

Distributed by: CVS Pharmacy, Inc.
One CVS Drive, Woonsocket, RI 02895
© 2024 CVS/pharmacy
CVS.com® 1-800-SHOP CVS

Made in India

PACKAGE LABEL-PRINCIPAL DISPLAY PANEL -10 mg (24 Orally Disintegrating Tablets) Blister Carton

CVS
Health®
Compare to the active
ingredient in Zyrtec® Allergy*
Indoor & Outdoor Allergies
NDC 69842-234-76
Original Prescription Strength
Allergy Relief
CETIRIZINE HYDROCHLORIDE ORALLY
DISINTEGRATING TABLETS, USP 10 mg
Antihistamine
Dissolve Tabs
24 HOUR
24 hour relief of:

- Sneezing
- Runny nose
- Itchy, watery eyes
- Itchy throat or nose

Melts In Your Mouth
Orange Flavor
Actual Size
24 TABLETS